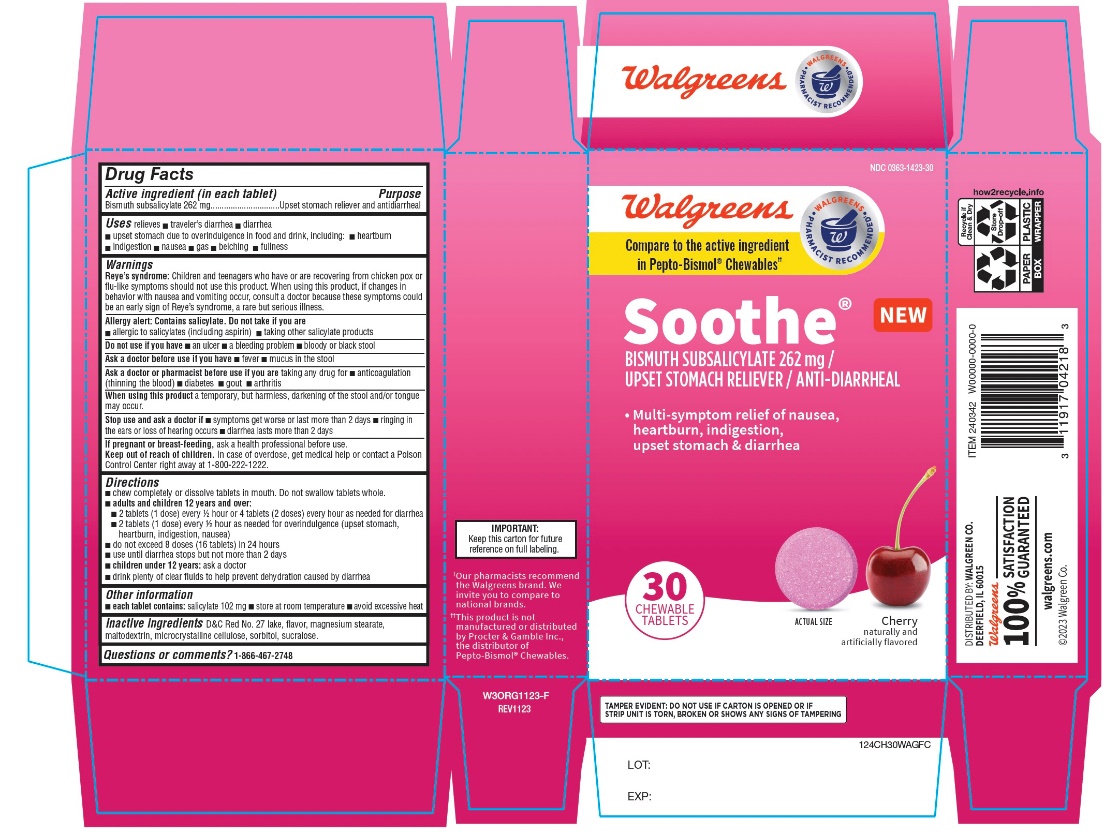 DRUG LABEL: Walgreen Stomach Relief
NDC: 0363-1423 | Form: TABLET, CHEWABLE
Manufacturer: WALGREENS CO.
Category: otc | Type: HUMAN OTC DRUG LABEL
Date: 20251125

ACTIVE INGREDIENTS: BISMUTH SUBSALICYLATE 262 mg/1 1
INACTIVE INGREDIENTS: D&C RED NO. 27; MAGNESIUM STEARATE; MALTODEXTRIN; MICROCRYSTALLINE CELLULOSE; SORBITOL; SUCRALOSE

Walgreen’s Stomach Relief Bismuth Subsalicylate 262 mg 30 Chewable Tablets

Active ingredient (in each tablet)

Bismuth subsalicylate 262 mg

Purpose

Upset stomach reliever and antidiarrheal

Uses

relieves:

- travelers’ diarrhea
- diarrhea
- upset stomach due to overindulgence in food and drink, including:
- heartburn
- indigestion
- nausea
- gas
- belching
- fullness

Warnings

Reye's syndrome:Children and teenagers who have or are recovering from chicken pox or flu-like symptoms should not use this product. When using this product, if changes in behavior with nausea and vomiting occur, consult a doctor because these symptoms could be an early sign of Reye's syndrome, a rare but serious illness.

Allergy alert: Contains salicylate. Do not take if you are

- allergic to salicylates (including aspirin)
- taking other salicylate products

Do not use if you have

- an ulcer
- a bleeding problem
- bloody or black stool

Ask a doctor before use if you have

- fever
- mucus in the stool

Ask a doctor or pharmacist before use if you aretaking any drug for

- anticoagulation (thinning of the blood)
- diabetes
- gout
- arthritis

When using this product

a temporary, but harmless, darkening of the stool and/or tongue may occur.

Stop use and ask a doctor if

- symptoms get worse or last more than 2 days
- ringing in the ears or loss of hearing occurs
- diarrhea lasts more than 2 days

If pregnant or breast-feeding,ask a health professional before use .

Keep Out of Reach of Children

In case of overdose, get medical help or contact a Poison Control Center immediately at 1-800-222-1222

Directions

- chew completely or dissolve tablets in mouth. Do not swallow tablets whole.
- adults and children 12 years and over:
- 2 tablets (1 dose) every ½ hour or 4 tablets (2 doses) every hour as needed for diarrhea
- 2 tablets (1 dose) every ½ hour as needed for over indulgence (upset stomach, heartburn, indigestion, nausea.
- do not exceed 8 doses (16 tablets) in 24 hours
- use until diarrhea stops but not more than 2 days
- children under 12 years:ask a doctor
- drink plenty clear fluids to help prevent dehydration caused by diarrhea.

Other information

- each tablet contains:salicylate 102 mg
- store at room temperature.
- avoid excessive heat

TAMPER EVIDENT: DO NOT USE IF CARTON IS OPENED OR IF STRIP UNIT IS TORN, BROKEN OR SHOWS ANY SIGNS OF TAMPERING.

Inactive ingredients

D&C Red No.27 lake, flavor, magnesium stearate, maltodextrin, microcrystalline cellulose, sorbitol, sucralose.

Questions or comments?

1- 866-467-2748

Principal Display

NDC# 0363-1423-30

Compare to the active ingredient in Pepto-Bismol®Chewables*

Stomach Relief

chewable tablets

Bismuth Subsalicylate 262 mg

Upset Stomach Reliever / Antidiarrheal

5 Symptoms Digestive Relief:

- Heartburn
- Indigestion
- Nausea
- Upset Stomach
- Diarrhea

Cherry Flavor

Naturally and Artificially Flavored

30 chewable tablets

Distributed by:

IMPORTANT:Keep this carton for future reference on full labeling.

*This product is not manufactured or distributed by Procter & Gamble Inc., the distributor of Pepto-Bismol® Chewables.